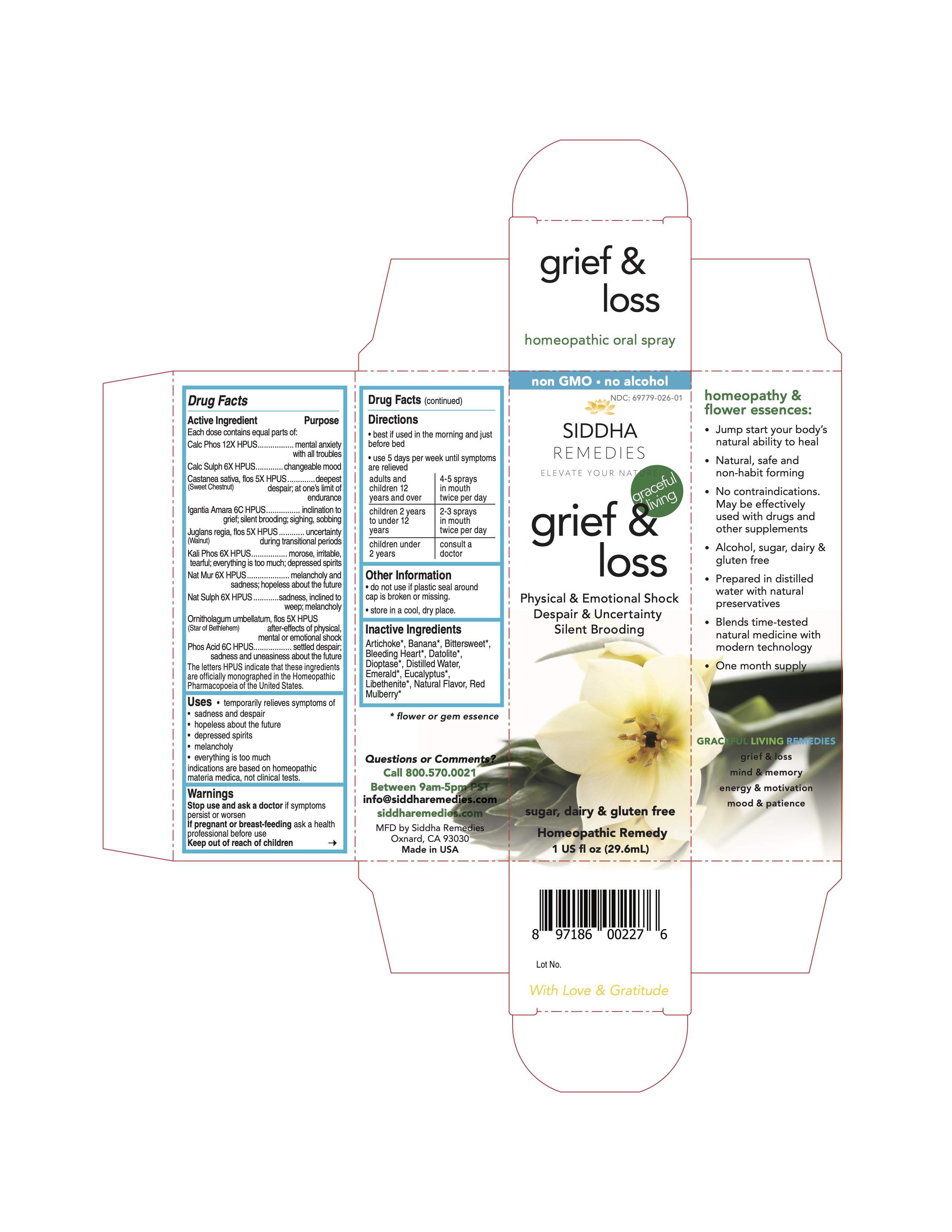 DRUG LABEL: grief and loss
NDC: 69779-026 | Form: SPRAY
Manufacturer: Siddha Flower Essences LLC
Category: homeopathic | Type: HUMAN OTC DRUG LABEL
Date: 20251231

ACTIVE INGREDIENTS: TRIBASIC CALCIUM PHOSPHATE 12 [hp_X]/29.6 mL; CALCIUM SULFATE ANHYDROUS 6 [hp_X]/29.6 mL; CASTANEA SATIVA FLOWER 5 [hp_X]/29.6 mL; STRYCHNOS IGNATII SEED 6 [hp_C]/29.6 mL; JUGLANS REGIA FLOWERING TOP 5 [hp_X]/29.6 mL; DIBASIC POTASSIUM PHOSPHATE 6 [hp_X]/29.6 mL; SODIUM CHLORIDE 6 [hp_X]/29.6 mL; SODIUM SULFATE 6 [hp_X]/29.6 mL; ORNITHOGALUM UMBELLATUM FLOWERING TOP 5 [hp_X]/29.6 mL; PHOSPHORIC ACID 6 [hp_C]/29.6 mL
INACTIVE INGREDIENTS: ARTICHOKE; BANANA; BITTERSWEET, UNSPECIFIED; LAMPROCAPNOS SPECTABILIS FLOWER; EUCALYPTUS GLOBULUS LEAF; WATER; MORUS RUBRA WHOLE

Active Ingredient

Each dose contains equal parts of:

Calc Phos 12X HPUS

Calc Sulph 6X HPUS

Castanea sativa, flos (sweet chestnut) 5X HPUS

Igantia Amara 6C HPUS

Juglans regia, flos (Walnut) 5X HPUS

Kali Phos 6X HPUS

Nat Mur 6X HPUS

Nat Sulph 6X HPUS

Ornitholagum umbellatum, flow (Star of Bethlehem) 5X HPUS

Phos Acid 6C HPUS

Purpose

Each dose contains equal parts of:

Calc Phos 12X HPUS.................................................................mental anxiety with all troubles

Calc Sulph 6X HPUS.................................................................changeable mood

Castanea sativa, flos (sweet chestnut) 5X HPUS...........................deepest despair; at one's limit of endurance

Igantia Amara 6C HPUS............................................................inclination to grief; silent brooding; sighing, sobbing

Juglans regia, flos (Walnut) 5X HPUS.........................................uncertainty during transitional periods

Kali Phos 6X HPUS...................................................................morose, irritable, tearful; verything is too much; depressed spirites

Nat Mur 6X HPUS....................................................................melancholy and sadness; hopeless about the future

Nat Sulph 6X HPUS..................................................................sadness, incined to weep; melancholy

Ornitholagum umbellatum, flow (Star of Bethlehem) 5X HPUS.......after-effects of physical, mental or emotional shock

Phos Acid 6C HPUS..................................................................settled despair; sadness and uneasiness about the future

Uses

temporarily relieves symptoms of

- sadness and despair
- hopeless about the future
- depressed soirits
- melancholy
- everything is too much

indications are based on homeopathic materia medica, not clinical tests.

Uses

Stop use and ask a doctor if symptoms persist or worsen

PREGNANCY OR BREAST FEEDING

If pregnant or breast-feeding ask a health professional before use

Keep out of reach of children

Directions

- best if used in the morning and just before bed
- use 5 days per week until symptoms are relieved

adults and children 12 years and over | 4-5 sprays in mouth twice per day
children 2 years to under 12 years | 2-3 sprays in mouth twice per day
children under 2 years | consult a doctor

Other Information

- do not use if plastic seal around cap is broken or missing.
- store in a cool, dry place.

Inactive Ingredients

Artichoke*, Banana*, Bittersweet*, Bleeding Heart*, Datolite*, Dioptase*, Emerald*, Eucalyptus*, Libethenite*, Natural Flavor, Purified Water, Red Mulberry*

*flower or gem essence

Questions or Comments?
Call 800.570.0021
Between 9am-5pm PST
info@siddhaflowers.com
siddhaflowers.com
MFD by Siddha Flower Essences
Oxnard, CA 93030
Made in USA

Side Panel

homeopathy and flower essences:

- Jump start your body's natural ability to heal
- Natural, safe and non-habit forming
- No contraindications. May be effectively used with drugs and other supplements
- Alcohol, sugar, dairy and gluten free
- Prepared in purified water with natural preservatives
- Blends time-tested natural medicine with modern technology
- One month supply

GRACEFUL AGING REMEDIES

grief & loss

mind & memory

energy & motivation

mood & patience

Principal Display Panel

non GMO - no alcohol
siddha cell salts + flower essences
grief & loss

Physical & EMotional Shock

Despair & Uncertainty

Silent Brooding

sugar, dairy & gluten free
Homeopathic Remedy
1 US fl oz (29.6mL)